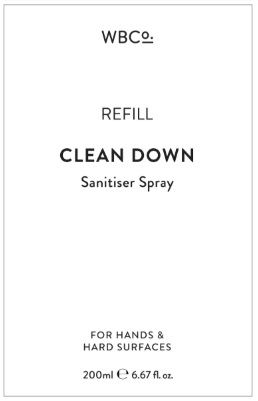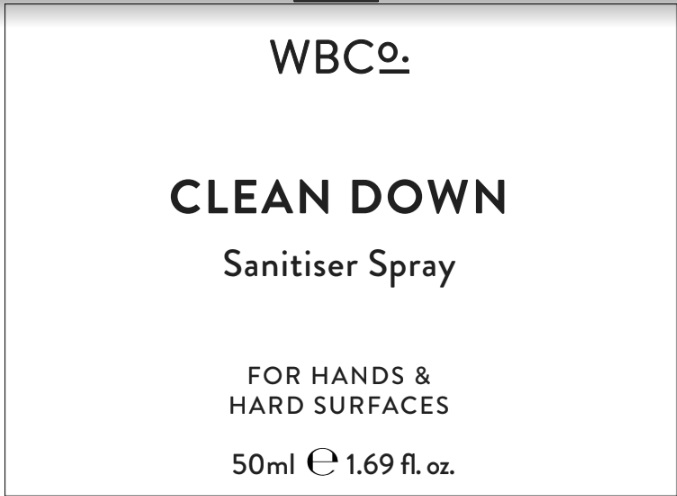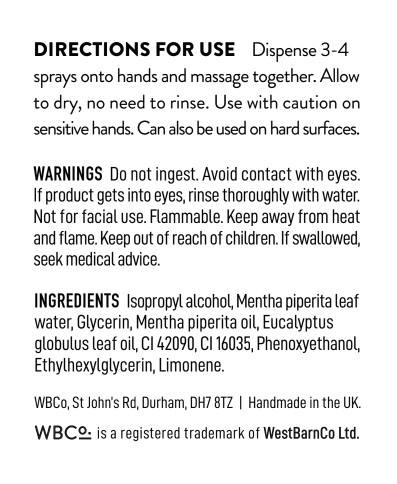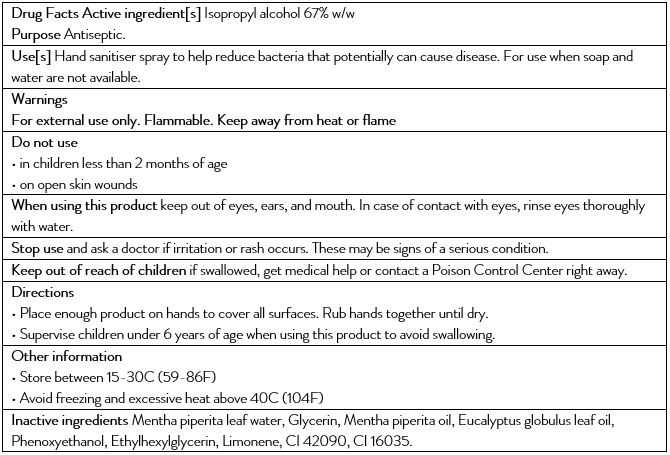 DRUG LABEL: Hand Sanitiser
NDC: 76916-167 | Form: SPRAY
Manufacturer: WESTBARNCO LTD
Category: otc | Type: HUMAN OTC DRUG LABEL
Date: 20201216

ACTIVE INGREDIENTS: ISOPROPYL ALCOHOL 0.67 mL/50 mL
INACTIVE INGREDIENTS: FD&C BLUE NO. 1 0.000028 mL/50 mL; PEPPERMINT OIL 0.0008 mL/50 mL; PHENOXYETHANOL 0.0000108 mL/50 mL; WATER 0.001135 mL/50 mL; FD&C RED NO. 40 0.000025 mL/50 mL; GLYCERIN 0.1 mL/50 mL; EUCALYPTUS OIL 0.0008 mL/50 mL; ETHYLHEXYLGLYCERIN 0.0000012 mL/50 mL; MENTHA PIPERITA LEAF 0.2272 mL/50 mL

Active Ingredient(s)

Isopropyl Alcohol 67% w/w

Purpose

Antiseptic

Use(s)

Hand sanitiser spray to help reduce bacteria that potentially can cause disease. For use when soap and water are not available.

Warnings

For external use only. Flammable. Keep away from heat or flame

Do not use

• in children less than 2 months of age

• on open skin wounds

When using this product

keep out of eyes, ears, and mouth. In case of contact with eyes, rinse eyes thoroughly with water.

Stop use

if irritation or rash occurs. These may be signs of a serious condition.

Keep out of reach of children

If swallowed, get medical help or contact a Poison Control Center right away.

Directions

• Place enough product on hands to cover all surfaces. Rub hands together until dry.

• Supervise children under 6 years of age when using this product to avoid swallowing.

Dosage

wet hands thoroughly with product and allow to dry without wiping

Other Information

• Store between 15-30C (59-86F)

• Avoid freezing and excessive heat above 40C (104F)

Inactive ingredients

Mentha piperita leaf water, Glycerin, Mentha piperita oil, Eucalyptus globulus leaf oil, Phenoxyethanol, Ethylhexylglycerin, Limonene, CI 42090, CI 16035.

PACKAGE LABEL

50ml. 76916-167-15

PACKAGE LABEL

200ml. 76916-167-12